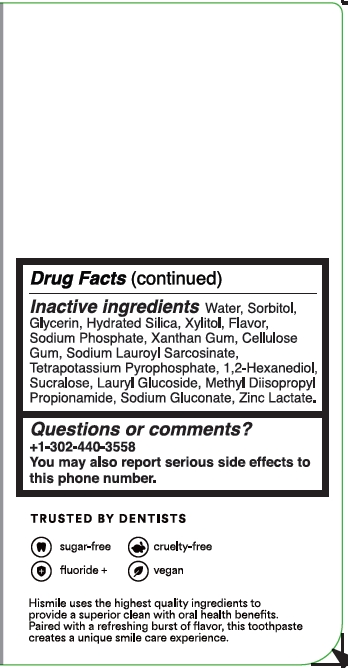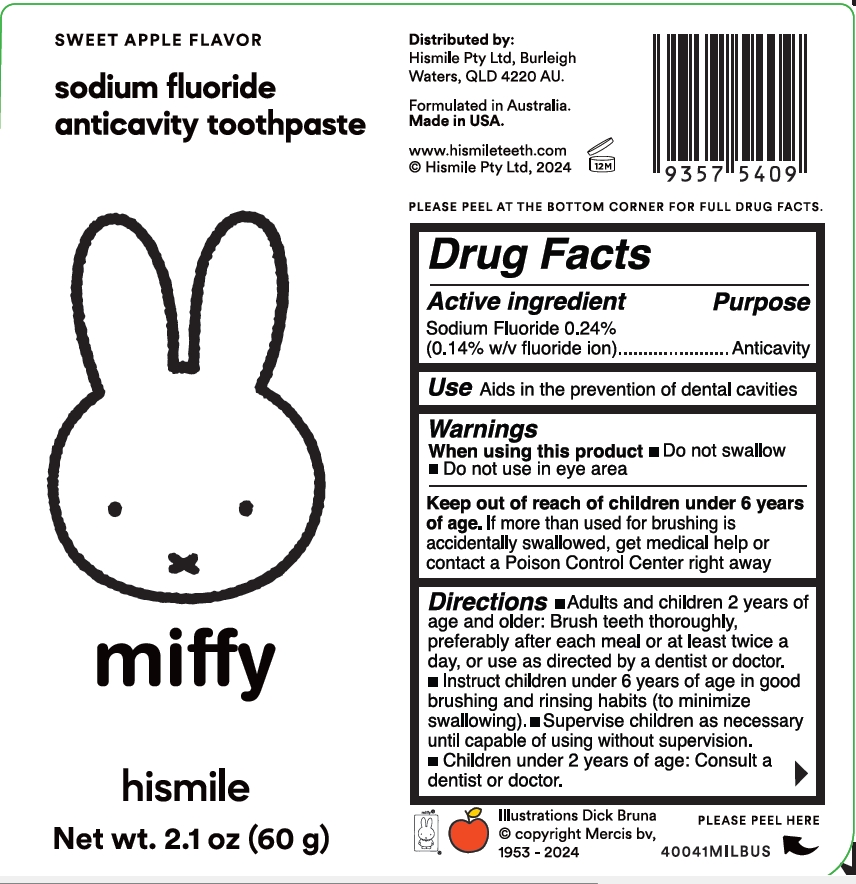 DRUG LABEL: Hismile Miffy Sweet Apple Flavor Sodium Fluoride Anticavity Toothpast
NDC: 83013-333 | Form: GEL
Manufacturer: Hismile Pty Ltd
Category: otc | Type: HUMAN OTC DRUG LABEL
Date: 20250313

ACTIVE INGREDIENTS: SODIUM FLUORIDE 0.243 g/100 g
INACTIVE INGREDIENTS: SODIUM PHOSPHATE; SUCRALOSE; LAURYL GLUCOSIDE; SODIUM GLUCONATE; HYDRATED SILICA; GLYCERIN; TETRAPOTASSIUM PYROPHOSPHATE; ZINC LACTATE; XYLITOL; WATER; SORBITOL; SODIUM LAUROYL SARCOSINATE; 1,2-HEXANEDIOL; XANTHAN GUM; CELLULOSE GUM; METHYL DIISOPROPYL PROPIONAMIDE

Hismile Miffy Sweet Apple Flavor Sodium Fluoride Anticavity Toothpaste

Active ingredient

Sodium Fluoride 0.24%

(0.14% w/v fluoride ion)

Purpose

Anticavity

Use

Aids in the prevention of dental cavities

Warnings

When using this product

Do not swallow

Do not use in eye area

Keep out of reach of children under 6 years of age

If more than used for brushing is accidentally swallowed, get medical help or contact a Poison Control Center right away

Directions

- Adults and children 2 years of age and older: Brush teeth thoroughly, preferably after each meal or at least twice a day, or use as directed by a dentist or doctor.
- Instruct children under 6 years of age in good brushing and rinsing habits (to minimize swallowing).
- Supervise children as necessary until capable of using without supervision.
- Children under 2 years of age: Consult a dentist or doctor.

Inactive ingredients

Water

Sorbitol

Glycerin

Hydrated Silica

Xylitol

Sodium Phosphate

Xanthan Gum

Cellulose Gum

Sodium Lauroyl Sarcosinate

Tetrapotassium Pyrophosphate

1,2-Hexanediol

Sucralose

Lauryl Glucoside

Methyl Diisopropyl Propionamide

Sodium Gluconate

Zinc Lactate